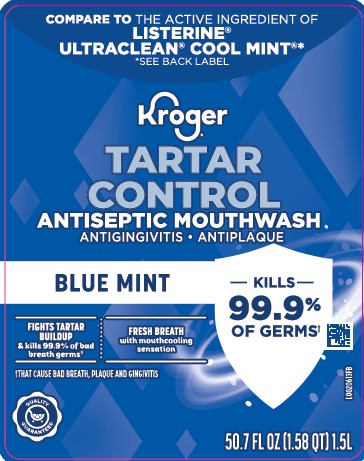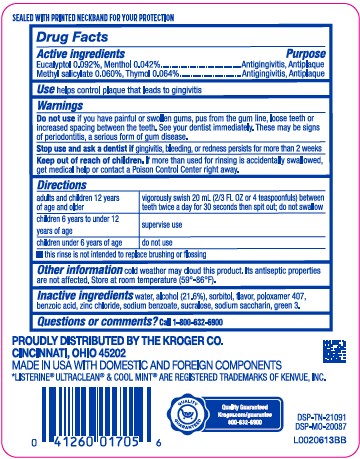 DRUG LABEL: Tartar control plus
NDC: 30142-855 | Form: MOUTHWASH
Manufacturer: The Kroger Co.
Category: otc | Type: HUMAN OTC DRUG LABEL
Date: 20260227

ACTIVE INGREDIENTS: EUCALYPTOL 0.92 mg/1 mL; MENTHOL 0.42 mg/1 mL; METHYL SALICYLATE 0.6 mg/1 mL; THYMOL 0.64 mg/1 mL
INACTIVE INGREDIENTS: WATER; ALCOHOL; SORBITOL; POLOXAMER 407; BENZOIC ACID; ZINC CHLORIDE; SODIUM BENZOATE; SUCRALOSE; SACCHARIN SODIUM; FD&C GREEN NO. 3

Kroger 855.000/855AC
Tartar Control Plus Antiseptic Mouth Rinse, Blue Mint

Tamper Evident Statement

SEALED WITH PRINTED NECKBAND FOR YOUR PROTECTION

Active ingredient

Eucalyptol 0.092%

Menthol 0.042%

Methyl salicylate 0.060%

Thymol 0.064%

Purpose

Antigingivitis, antiplaque

Use

helps control plaque that leads to gingivitis

Warnings

For this product

Do not use

if you have painful or swollen gums, pus from the gum line, loose teeth or increased spacing between the teeth. See your dentist immediately. These may be signs of periodontitis, a serious form of gum disease.

Stop use and ask a dentist if

gingivitis, bleeding, or redness persists for more than 2 weeks.

Keep out of reach of children.

If more than used for rinsing is accidentally swallowed, get medical help or contact a Poison Control Center right away.

Directions

adults and children 12 years of age and older - vigorously swish 20 mL (2/3 FL OZ or 4 teaspoonfuls) between teeth twice a day for 30 seconds then spit out; do not swallow

children 6 years to under 12 years of age - supervise use

children under 6 years of age - do not use

- this rinse is not intended to replace brushing or flossing

Other information

cold weather may cloud this product. Its antiseptic properties are not affected. Store at room temperature (59°-86°F).

Inactive ingredients

water, alcohol (21.6%), sorbitol, flavor, poloxamer 407, benzoic acid, zinc chloride, sodium benzoate, sucralose, sodium saccharin, green 3

Questions?

Call 1-800-632-6900

ADVERSE REACTION

PROUDLY DISTRIBUTED BY THE KROGER CO.

CINCINNATI, OH 45202

MADE IN USA WITH DOMESTIC AND FOREIGN COMPONENTS

QUALITY GUARANTEED

Kroger.com/guarantee

800-632-6900

DSP-TN-21091

DSP-MO-20087

Disclaimer

*Listerine®Ultraclean® & Cool Mint®are registered trademarks of Kenvue, Inc.

principal display panel

Compare to the active ingredient of Listerine®Ultraclean®Cool Mint®*

*SEE BACK LABEL

Kroger®

Tartar Control

Antiseptic Mouthwash

ANTIGINGIVITIS/ANTIPLAQUE

BLUE MINT

KILLS 99.9 OF GERMS†

FIGHTS TARTAR BUILDUP & kills 99.9% of bad breath germs†

FRESH BREATH with mouthcooling sensation

†THAT CAUSE BAD BREATH, PLAQUE AND GINGIVITIS

QUALITY GUARANTEED

50.7 FL OZ (1.58 QT) 1.5 L